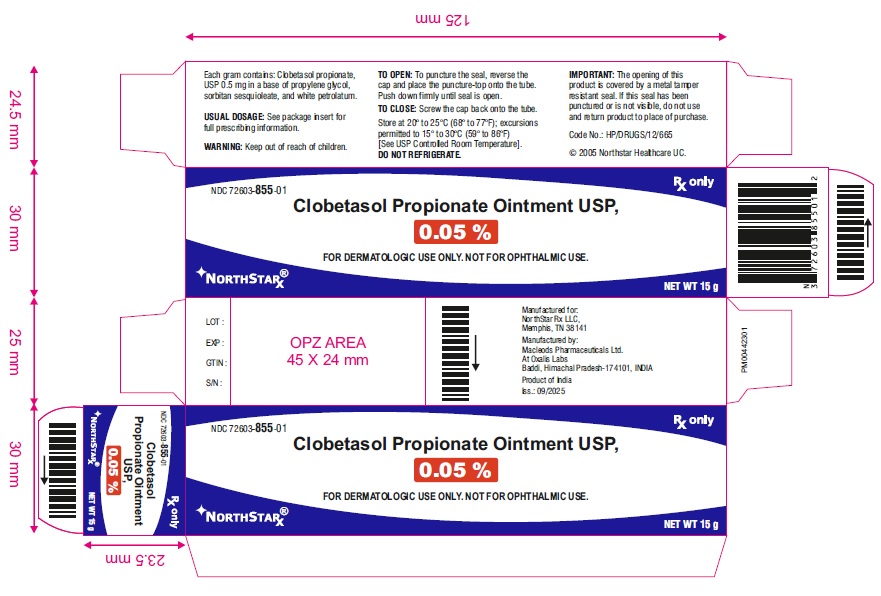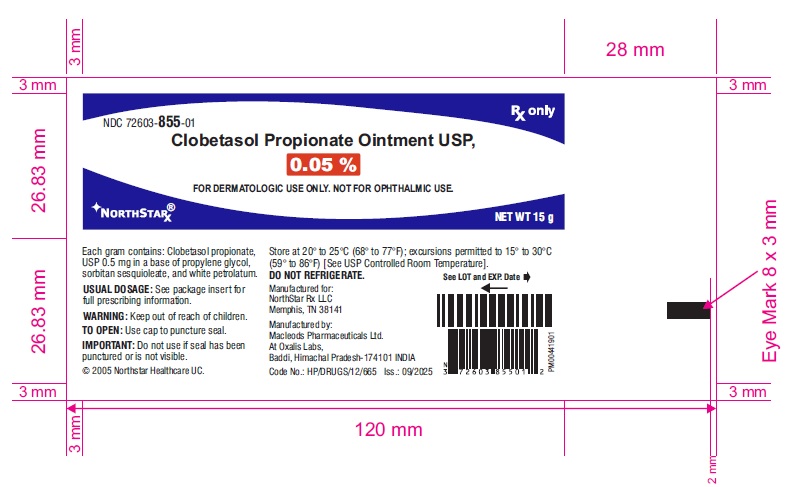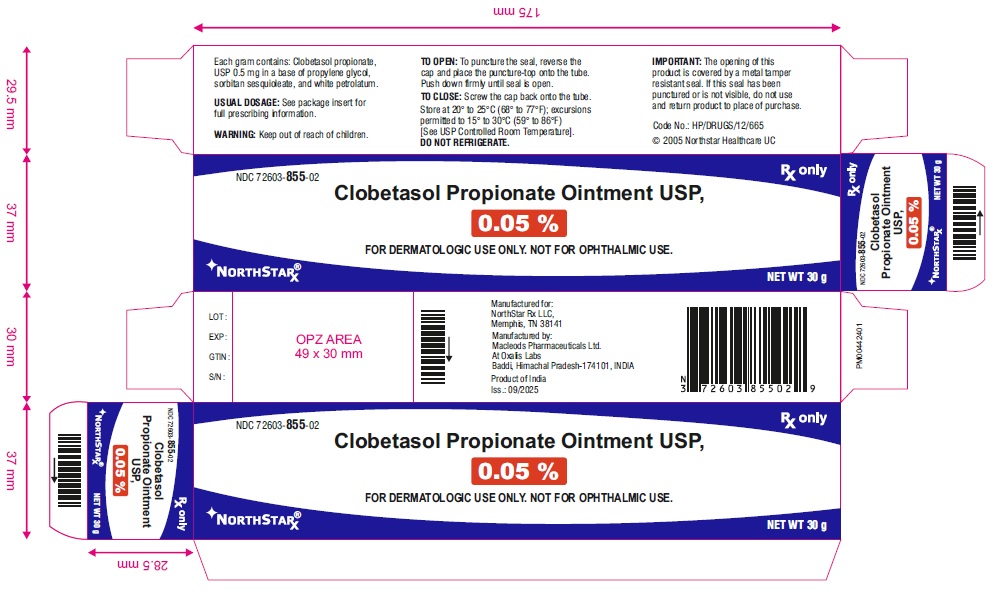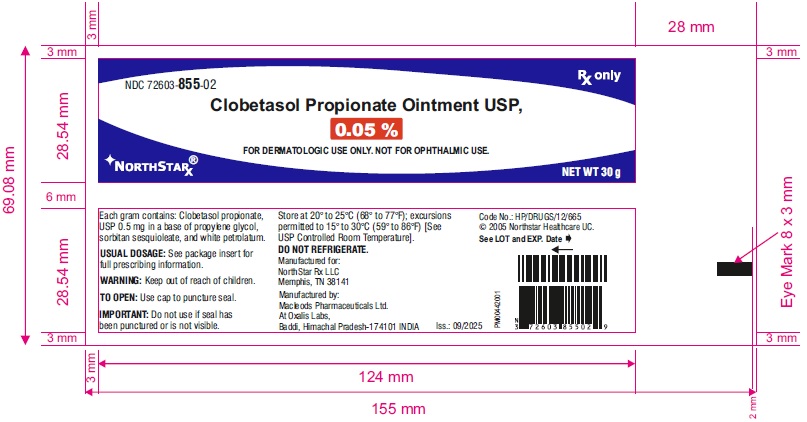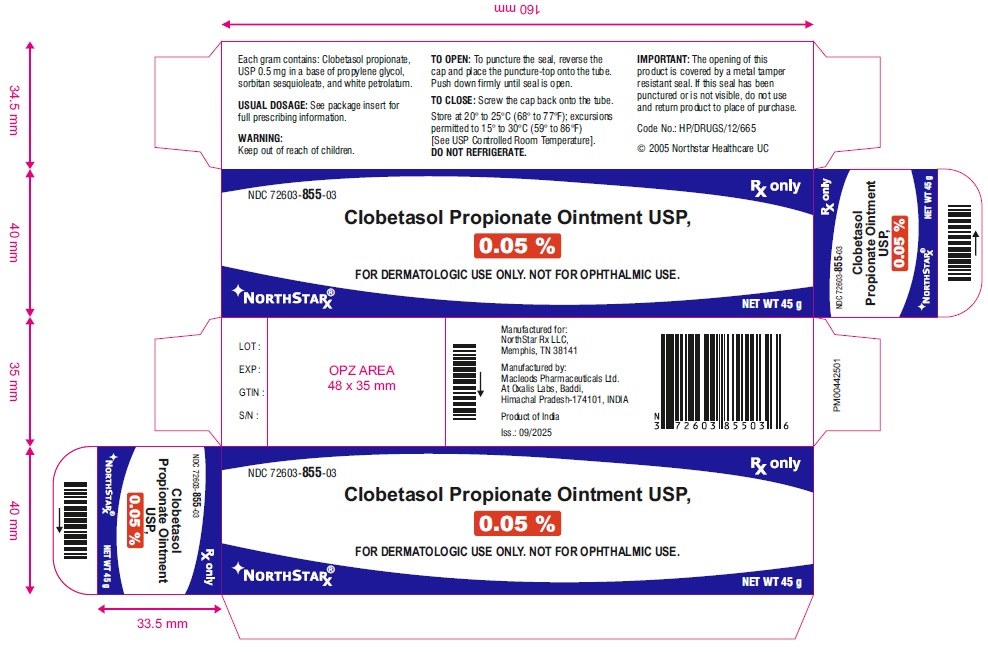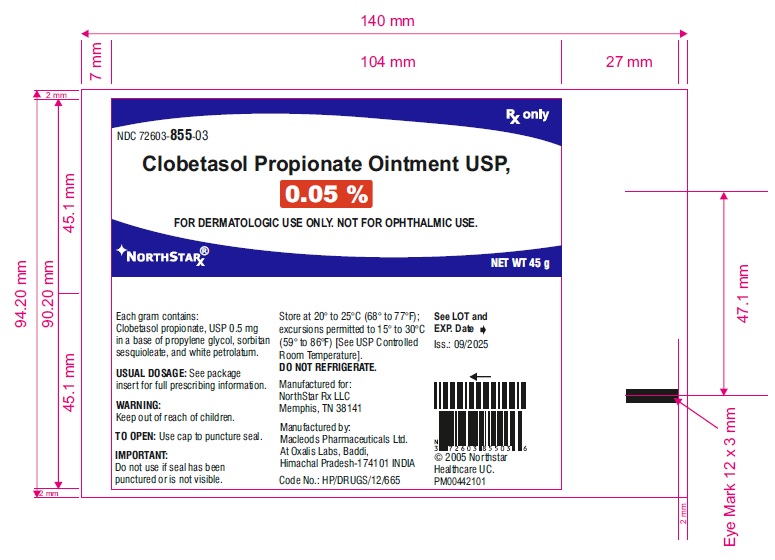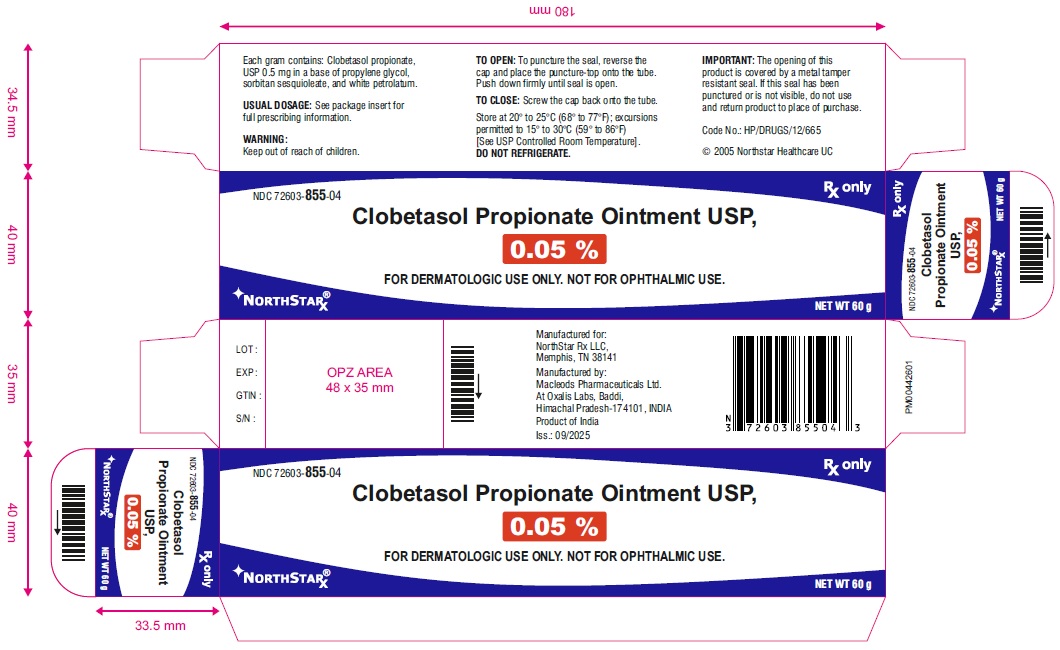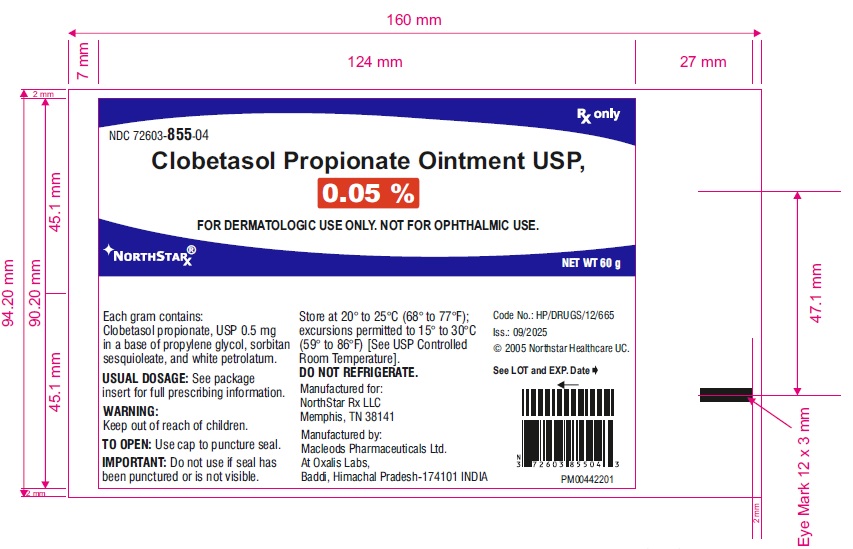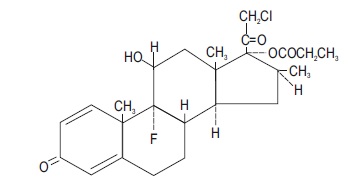 DRUG LABEL: Clobetasol Propionate
NDC: 72603-855 | Form: OINTMENT
Manufacturer: NorthStar RxLLC
Category: prescription | Type: Human Prescription Drug Label
Date: 20260211

ACTIVE INGREDIENTS: CLOBETASOL PROPIONATE 0.5 mg/1 g
INACTIVE INGREDIENTS: PROPYLENE GLYCOL; SORBITAN SESQUIOLEATE; PETROLATUM

Clobetasol Propionate Ointment USP, 0.05%
FOR TOPICAL DERMATOLOGIC USE ONLY NOT FOR OPHTHALMIC, ORAL, OR INTRAVAGINAL USE

DESCRIPTION

Clobetasol propionate ointment USP, contain the active compound clobetasol propionate, a synthetic corticosteroid, for topical dermatologic use. Clobetasol, an analog of prednisolone, has a high degree of glucocorticoid activity and a slight degree of mineralocorticoid activity.
Chemically, clobetasol propionate is (11β, 16 β)-21-chloro-9-fluoro-11-hydroxy-16-methyt-17-(1-oxopropoxy)-pregna-1,4-diene-3,20-dione, and it has the following structural formula:

Clobetasol propionate has the empirical formula C25H32CIF05 and a molecular weight of 467. It is a white to cream-colored crystalline powder insoluble in water.
Clobetasol propionate ointment USP, clobetasol propionate 0.5 mg/g in a base of propylene glycol, sorbitan sesquioleate, and white petrolatum.

CLINICAL PHARMACOLOGY

Like other topical corticosteroids, clobetasol propionate has anti-inflammatory, antipruritic, and vasoconstrictive properties. The mechanism of the anti-inflammatory activity of the topical steroids, in general, is unclear.
However, corticosteroids are thought to act by the induction of phospholipase A2 inhibitory proteins, collectively called lipocortins. It is postulated that these proteins control the biosynthesis of potent mediators of inflammation such as prostaglandins and leukotrienes by inhibiting the release of their common precursor, arachidonic acid. Arachidonic acid is released from membrane phospholipids by phospholipase A2.

Pharmacokinetics

The extent of percutaneous absorption of topical corticosteroids is determined by many factors, including the vehicle and the integrity of the epidermal barrier. Occlusive dressing with hydrocortisone for up to 24 hours has not been demonstrated to increase penetration; however, occlusion of hydrocortisone for 96 hours markedly enhances penetration.

Topical corticosteroids can be absorbed from normal intact skin. Inflammation and/or other disease processes in the skin may increase percutaneous absorption.

Studies performed with clobetasol propionate ointment indicate that they are in the super-high range of potency as compared with other topical corticosteroids.

INDICATIONS AND USAGE

Clobetasol propionate ointment is super-high potency corticosteroid formulations indicated for the relief of the inflammatory and pruritic manifestations of corticosteroid- responsive dermatoses. Treatment beyond 2 consecutive weeks is not recommended, and the total dosage should not exceed 50 g/week because of the potential for the drug to suppress the hypothalamic-pituitary-adrenal (HPA) axis. Use in pediatric patients under 12 years of age is not recommended.
As with other highly active corticosteroids, therapy should be discontinued when control has been achieved. If no improvement is seen within 2 weeks, reassessment of the diagnosis may be necessary.

CONTRAINDICATIONS

Clobetasol propionate ointment is contraindicated in those patients with a history of hypersensitivity to any of the components of the preparations.

PRECAUTIONS

General:

Clobetasol propionate ointment should not be used in the treatment of rosacea or perioral dermatitis, and should not be used on the face, groin, or axillae.
Systemic absorption of topical corticosteroids can produce reversible HPA axis suppression with the potential for glucocorticosteroid insufficiency after withdrawal from treatment.
Manifestations of Cushing's syndrome, hyperglycemia, and glucosuria can also be produced in some patients by systemic absorption of topical corticosteroids while on therapy.
Patients applying a topical steroid to a large surface area or to areas under occlusion should be evaluated periodically for evidence of HPA axis suppression. This may be done by using the ACTH stimulation, A.M. plasma cortisol, and urinary free cortisol tests. Patients receiving super-potent corticosteroids should not be treated for more than 2 weeks at a time, and only small areas should be treated at any one time due to the increased risk of HPA suppression.
Clobetasol propionate ointment produced HPA axis suppression when used at doses as low as 2 g/day for 1 week in patients with eczema.
If HPA axis suppression is noted, an attempt should be made to withdraw the drug, to reduce the frequency of application, or to substitute a less potent corticosteroid. Recovery of HPA axis function is generally prompt upon discontinuation of topical corticosteroids. Infrequently, signs and symptoms of glucocorticosteroid insufficiency may occur that require supplemental systemic corticosteroids. For information on systemic supplementation, see prescribing information for those products.
Pediatric patients may be more susceptible to systemic toxicity from equivalent doses due to their larger skin surface to body mass ratios (see PRECAUTIONS: Pediatric Use).
If irritation develops, clobetasol propionate ointment should be discontinued and appropriate therapy instituted. Allergic contact dermatitis with corticosteroids is usually diagnosed by observing a failure to heal rather than noting a clinical exacerbation as with most topical products not containing corticosteroids. Such an observation should be corroborated with appropriate diagnostic patch testing.
If concomitant skin infections are present or develop, an appropriate antifungal or antibacterial agent should be used.
If a favorable response does not occur promptly, use of clobetasol propionate ointment should be discontinued until the infection has been adequately controlled.

Information for Patients:

Patients using topical corticosteroids should receive the following information and instructions:

1. This medication is to be used as directed by the physician. It is for external use only. Avoid contact with the eyes.
2. This medication should not be used for any disorder other than that for which it was prescribed.
3. The treated skin area should not be bandaged, otherwise covered, or wrapped so as to be occlusive unless directed by the physician.
4. Patients should report any signs of local adverse reactions to the physician.

Laboratory Tests:

The following tests may be helpful in evaluating patients for HPA axis suppression:
ACTH stimulation test
A.M. plasma cortisol test
Urinary free cortisol test

Carcinogenesis, Mutagenesis, Impairment of Fertility:

Long-term animal studies have not been performed to evaluate the carcinogenic potential of clobetasol propionate.
Studies in the rat following subcutaneous administration at dosage levels up to 50 mcg/kg per day revealed that the females exhibited an increase in the number of resorbed embryos and a decrease in the number of living fetuses at the highest dose.
Clobetasol propionate was nonmutagenic in 3 different test systems: the Ames test, the Saccharomyces cerevisiae gene conversion assay, and the E coli B WP2 fluctuation test.

Pregnancy: Teratogenic Effects:

Corticosteroids have been shown to be teratogenic in laboratory animals when administered systemically at relatively low dosage levels. Some corticosteroids have been shown to be teratogenic after dermal application to laboratory animals.
Clobetasol propionate has not been tested for teratogenicity when applied topically; however, it is absorbed percutaneously, and when administered subcutaneously it was a significant teratogen in both the rabbit and mouse. Clobetasol propionate has greater teratogenic potential than steroids that are less potent.
Teratogenicity studies in mice using the subcutaneous route resulted in fetotoxicity at the highest dose tested (1 mg/kg) and teratogenicity at all dose levels tested down to 0.03 mg/kg. These doses are approximately 1.4 and 0.04 times, respectively, the human topical dose of clobetasol propionate ointment. Abnormalities seen included cleft palate and skeletal abnormalities.
In rabbits, clobetasol propionate was teratogenic at doses of 3 and 10 mcg/kg. These doses are approximately 0.02 and 0.05 times, respectively, the human topical dose of clobetasol propionate ointment. Abnormalities seen included cleft palate, cranioschisis, and other skeletal abnormalities.
There are no adequate and well-controlled studies of the teratogenic potential of clobetasol propionate in pregnant women. Clobetasol propionate ointment should be used during pregnancy only if the potential benefit justifies the potential risk to the fetus.

Nursing Mothers:

Systemically administered corticosteroids appear in human milk and could suppress growth, interfere with endogenous corticosteroid production, or cause other untoward effects. It is not known whether topical administration of corticosteroids could result in sufficient systemic absorption to produce detectable quantities in human milk. Because many drugs are excreted in human milk, caution should be exercised when clobetasol propionate ointment is administered to a nursing woman.

Pediatric Use:

Safety and effectiveness of clobetasol propionate ointment in pediatric patients have not been established. Use in pediatric patients under 12 years of age is not recommended. Because of a higher ratio of skin surface area to body mass, pediatric patients are at a greater risk than adults of HPA axis suppression and Cushing's syndrome when they are treated with topical corticosteroids. They are therefore also at greater risk of adrenal insufficiency during or after withdrawal of treatment. Adverse effects including striae have been reported with inappropriate use of topical corticosteroids in infants and children.

HPA axis suppression, Cushing's syndrome, linear growth retardation, delayed weight gain, and intracranial hypertension have been reported in children receiving topical corticosteroids.

Manifestations of adrenal suppression in children include low plasma cortisol levels and an absence of response to ACTH stimulation. Manifestations of intracranial hypertension include bulging fontanelles, headaches, and bilateral papilledema.

Geriatric Use:

A limited number of patients at or above 65 years of age have been treated with clobetasol propionate ointment (n = 101) in US and non-US clinical trials. While the number of patients is too small to permit separate analysis of efficacy and safety, the adverse reactions reported in this population were similar to those reported by younger patients. Based on available data, no adjustment of dosage of clobetasol propionate ointment in geriatric patients is warranted.

ADVERSE REACTIONS

In controlled clinical trials, the most frequent adverse events reported for clobetasol propionate ointment were burning sensation, irritation, and itching in 0.5% of treated patients. Less frequent adverse reactions were stinging, cracking, erythema, folliculitis, numbness of fingers, skin atrophy, and telangiectasia.
Cushing's syndrome has been reported in infants and adults as a result of prolonged use of topical clobetasol propionate formulations.
The following additional local adverse reactions have been reported with topical corticosteroids, and they may occur more frequently with the use of occlusive dressings and higher potency corticosteroids. These reactions are listed in an approximately decreasing order of occurrence: dryness, acneiform eruptions, hypopigmentation, perioral dermatitis, allergic contact dermatitis, secondary infection, irritation, striae, and miliaria.

OVERDOSAGE

Topically applied clobetasol propionate ointment can be absorbed in sufficient amounts to produce systemic effects (see PRECAUTIONS).

DOSAGE AND ADMINISTRATION

Apply a thin layer of clobetasol propionate ointment USP, to the affected skin areas twice daily and rub in gently and completely (see INDICATIONS AND USAGE).
Clobetasol propionate ointment USP, is super-high potency topical corticosteroids; therefore, treatment should be limited to 2 consecutive weeks and amounts greater than 50 g/week should not be used.
As with other highly active corticosteroids, therapy should be discontinued when control has been achieved. If no improvement is seen within 2 weeks, reassessment of diagnosis may be necessary.
Clobetasol propionate ointment USP, should not be used with occlusive dressings.

Geriatric Use:
In studies where geriatric patients (65 years of age or older, see PRECAUTIONS) have been treated with clobetasol propionate ointment safety did not differ from that in younger patients; therefore, no dosage adjustment is recommended.

HOW SUPPLIED

Clobetasol propionate ointment USP, 0.05% is supplied in
15 g tube NDC 72603-855-01
30 g tube NDC 72603-855-02
45 g tube NDC 72603-855-03
60 g tube NDC 72603-855-04
Store at 20° to 25°C (68° to 77°F); excursions permitted to 15° to 30°C (59° to 86°F) [See USP Controlled Room Temperature].
DO NOT REFRIGERATE.

Manufactured for:

Northstar Rx LLC.

Memphis, TN 38141.

Toll number: 1-800-206-7821

Manufactured by:
Macleods Pharmaceuticals Ltd.
At Oxalis Labs

Baddi, Himachal Pradesh-174101, INDIA

Revised: February 2026

PACKAGE LABEL.PRINCIPAL DISPLAY PANEL

Clobetasol Propionate Ointment USP, 0.05% w/w
Pack Count: 15 g Tube
NDC 72603-855-01

Clobetasol Propionate Ointment USP, 0.05% w/w
Pack Count: 15 g Carton
NDC 72603-855-01

Clobetasol Propionate Ointment USP, 0.05% w/w
Pack Count: 30 g Tube
NDC 72603-855-02

Clobetasol Propionate Ointment USP, 0.05% w/w
Pack Count: 30 g Carton
NDC 72603-855-02

Clobetasol Propionate Ointment USP, 0.05% w/w
Pack Count: 45 g Tube
NDC 72603-855-03

Clobetasol Propionate Ointment USP, 0.05% w/w
Pack Count: 45 g Carton
NDC 72603-855-03

Clobetasol Propionate Ointment USP, 0.05% w/w
Pack Count: 60 g Tube
NDC 72603-855-04

Clobetasol Propionate Ointment USP, 0.05% w/w
Pack Count: 60 g Carton
NDC 72603-855-04